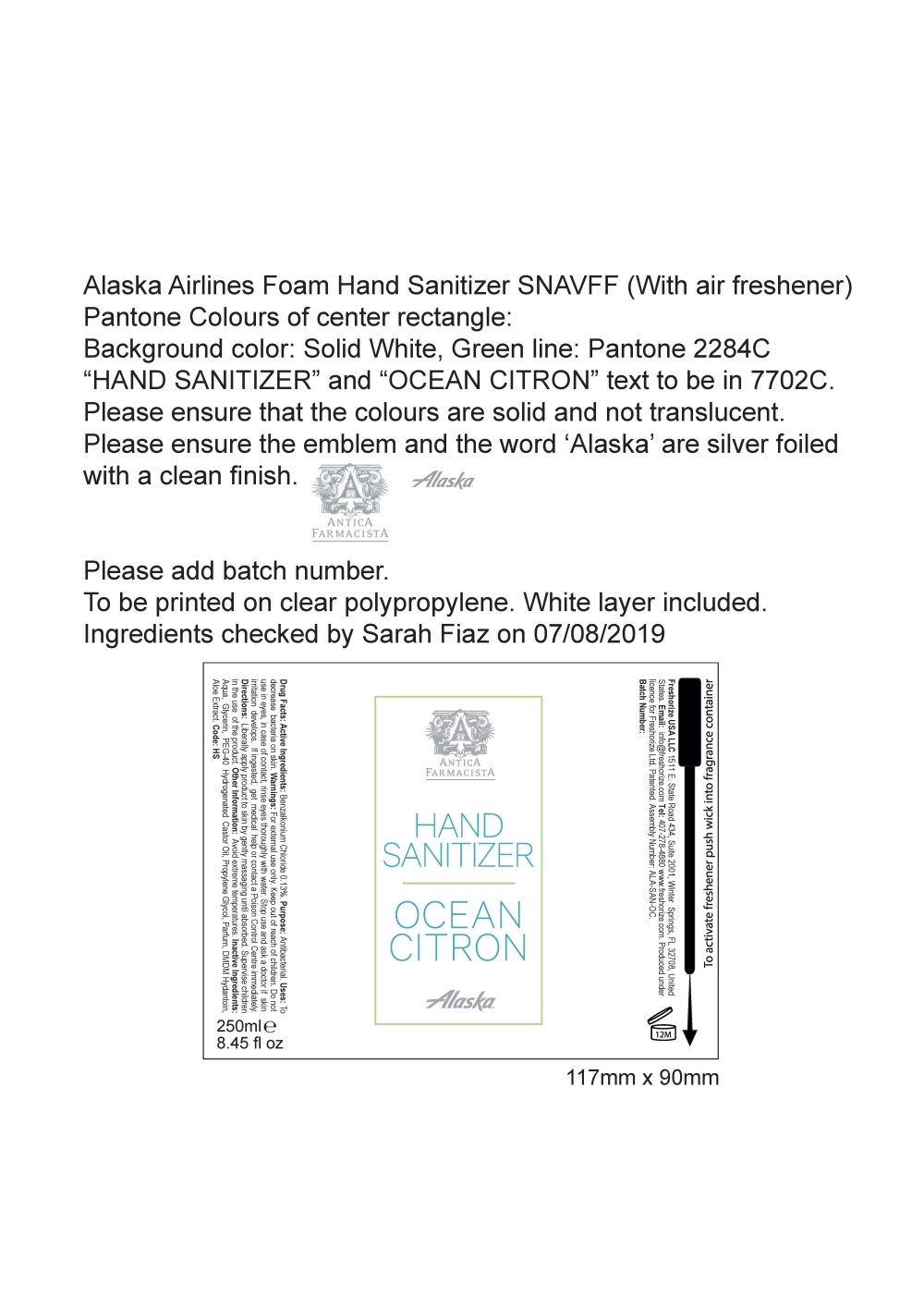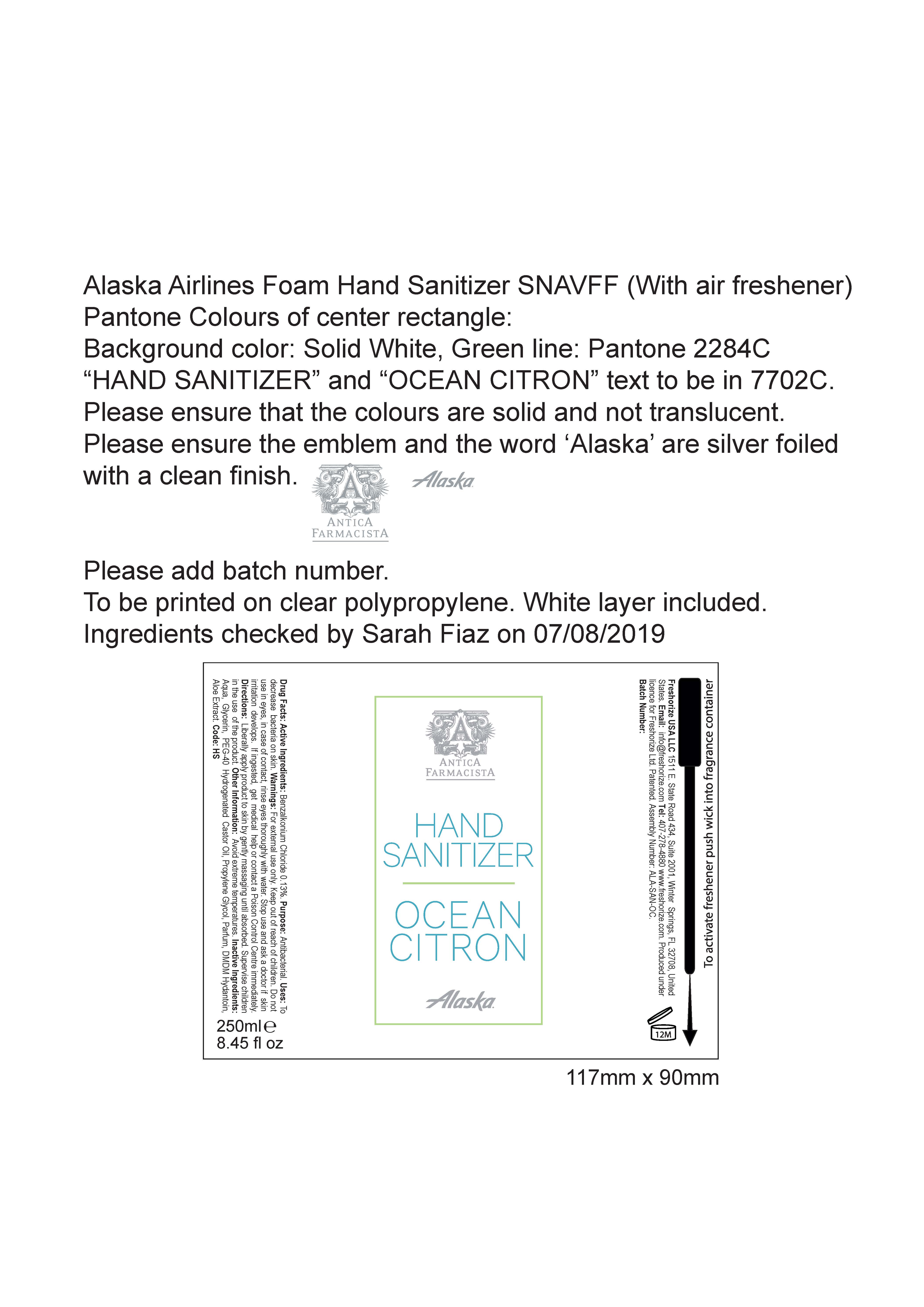 DRUG LABEL: Alaska Airlines
NDC: 52305-602 | Form: LIQUID
Manufacturer: Freshorize Ltd.
Category: otc | Type: HUMAN OTC DRUG LABEL
Date: 20251023

ACTIVE INGREDIENTS: BENZALKONIUM CHLORIDE 0.13 g/100 mL
INACTIVE INGREDIENTS: PROPYLENE 0.5 g/100 mL; WATER 97.05 g/100 mL; ALOE VERA LEAF 0.1 g/100 mL; DMDM HYDANTOIN 0.2 g/100 mL; GLYCERIN 3 g/100 mL; HYDROGENATED CASTOR OIL 0.75 g/100 mL

Alaska Airlines Alcohol Free Hand Sanitizer

Warnings:

For external use only.

Do not use in eyes. In case of contact, rinse eyes thoroughly with water.
Stop use and ask a doctor if skin irritation develops.
If ingested, get medical help or contact a Poison Control Center immediately.

Warnings:

Keep out of reach of children.

Directions:

Liberally apply product to skin by gently massaging until absorbed.
Supervise children in the use of this product.

Uses:

To decrease bacteria on the skin.

Purpose:

Antibacterial.

Drug facts:

Active Ingredients: Benzalkonium Chloride.

Inactive Ingredients:

Water (Aqua), Glycerin, PEG-40 Hydrogenated Castor Oil, DMDM Hydantoin, Propylene Glycol, Parfum, Aloe Barbadensis Leaf Extract

Other Information:

Avoid extreme temperatures.

Alaska Arilines Foam Hand Sanitizer

Alaska hand Sanitizer

Hand Sanitizer
Ocean Citron

This is a pump item with no dosage information. Most customers use 1-2 pumps.